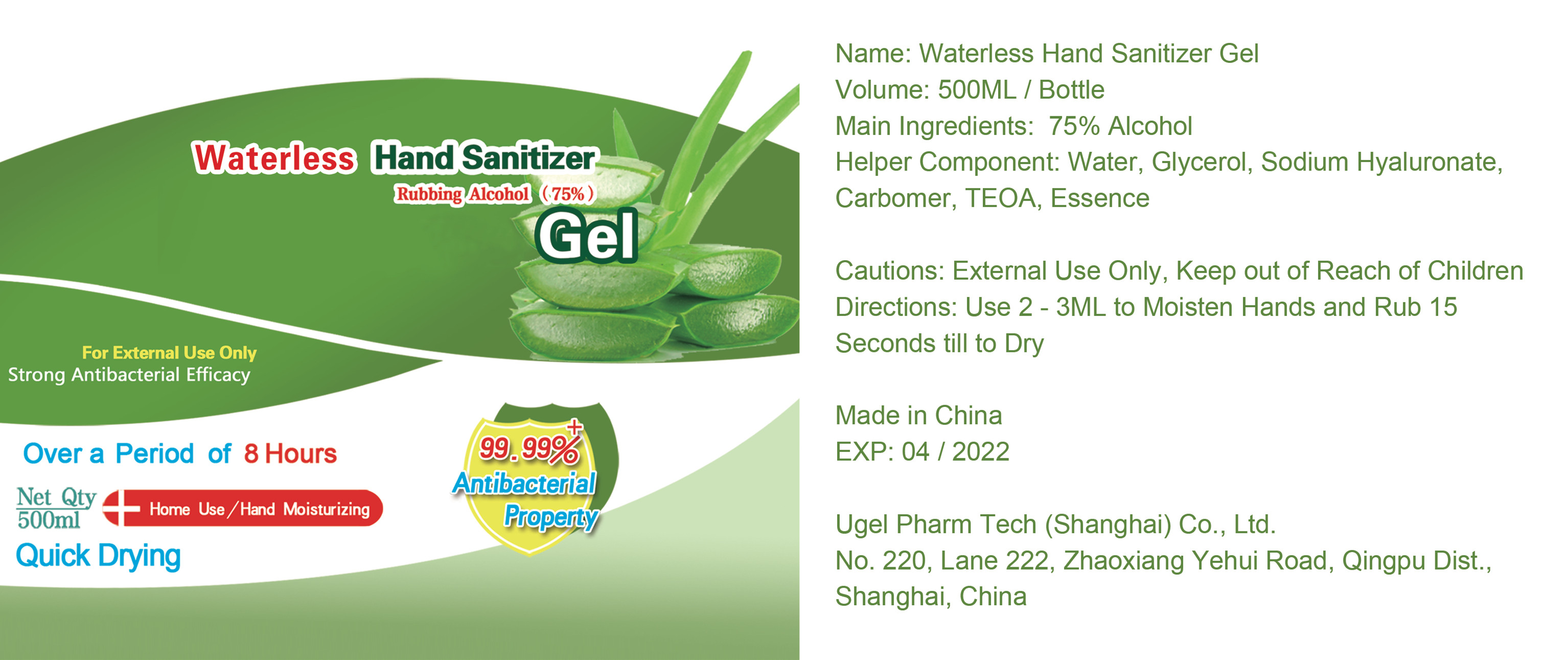 DRUG LABEL: Waterless Hand Sanitizer Gel
NDC: 55262-002 | Form: GEL
Manufacturer: Ugel Pharm Tech (Shanghai) Co., Ltd.
Category: otc | Type: HUMAN OTC DRUG LABEL
Date: 20200522

ACTIVE INGREDIENTS: ALCOHOL 375 mL/500 mL
INACTIVE INGREDIENTS: HYALURONATE SODIUM; WATER; CARBOMER HOMOPOLYMER, UNSPECIFIED TYPE; TROLAMINE; METHYL BENZOATE; GLYCERIN

DOSAGE AND ADMINISTRATION

Store in a cool and dry place

INACTIVE INGREDIENT

Water, Glycerol, Sodium Hyaluronate, Carbomer, TEOA, Essence

INDICATIONS AND USAGE

Use 2 - 3ML to Moisten Hands and Rub 15 Seconds till to Dry

ACTIVE INGREDIENT

Alcohol

keep out of reach of children

PURPOSE

Disinfection
Sterilization
No Rinseing

WARNINGS

External Use Only, Keep out of Reach of Children